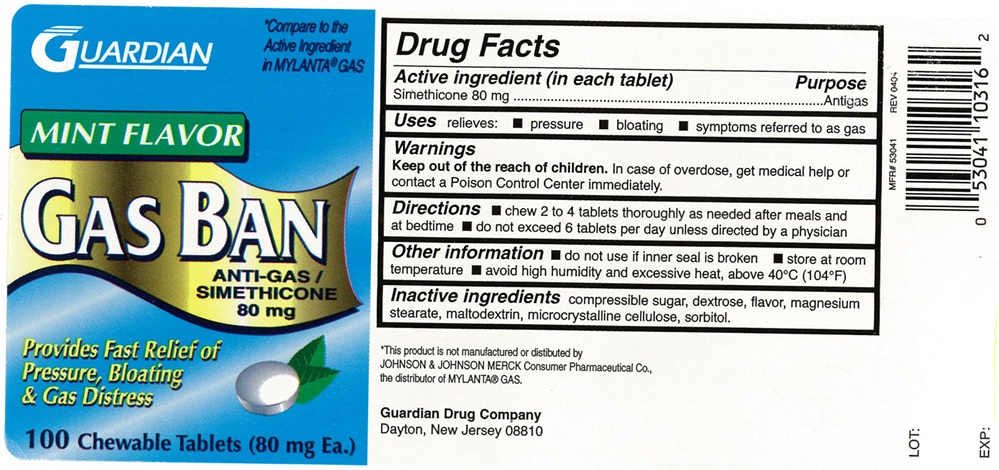 DRUG LABEL: Gas relief
NDC: 53041-103 | Form: TABLET, CHEWABLE
Manufacturer: Guardian Drug Company
Category: otc | Type: Human OTC Drug Label
Date: 20250206

ACTIVE INGREDIENTS: DIMETHICONE 80 mg/1 1
INACTIVE INGREDIENTS: SUGARCANE; MALTODEXTRIN; DEXTROSE, UNSPECIFIED FORM; MAGNESIUM STEARATE; MICROCRYSTALLINE CELLULOSE; SORBITOL

Gas Relief Chewable Tablets

ACTIVE INGREDIENT(in each tablet)

Simethicone 80 mg

PURPOSE

Antigas

USE(S)

relieves:

- pressure
- bloating
- symptoms referred to as gas

WARNINGS

.

KEEP OUT OF REACH OF CHILDREN

In case of overdose, get medical help or contact a Poison Control Center immediately.

DIRECTIONS

- chew 2 to 4 tablets thoroughly as needed after meals and at bedtime
- do not exceed 6 tablets per day unless directed by a physician

OTHER INFORMATION

- do not use if inner seal is broken
- store at room temperature
- avoid high humidity and excessive heat, above 40oC (104oF)

INACTIVE INGREDIENTS

compressible sugar, dextrose, flavor, magnesium stearate, maltodextrin, microcrystalline cellulose, sorbitol.

PRINCIPAL DISPLAY PANEL

GUARDIAN

NDC 53041-103-16

*Compare to the Active Ingredient in MYLANTA® GAS

MINT FLAVOR

GAS BAN

ANTI-GAS/
SIMETHICONE

80 mg
Provides Fast Relief of

Pressure, Bloating

& Gas Distress
100 Chewable Tablets (80 mg Ea.)